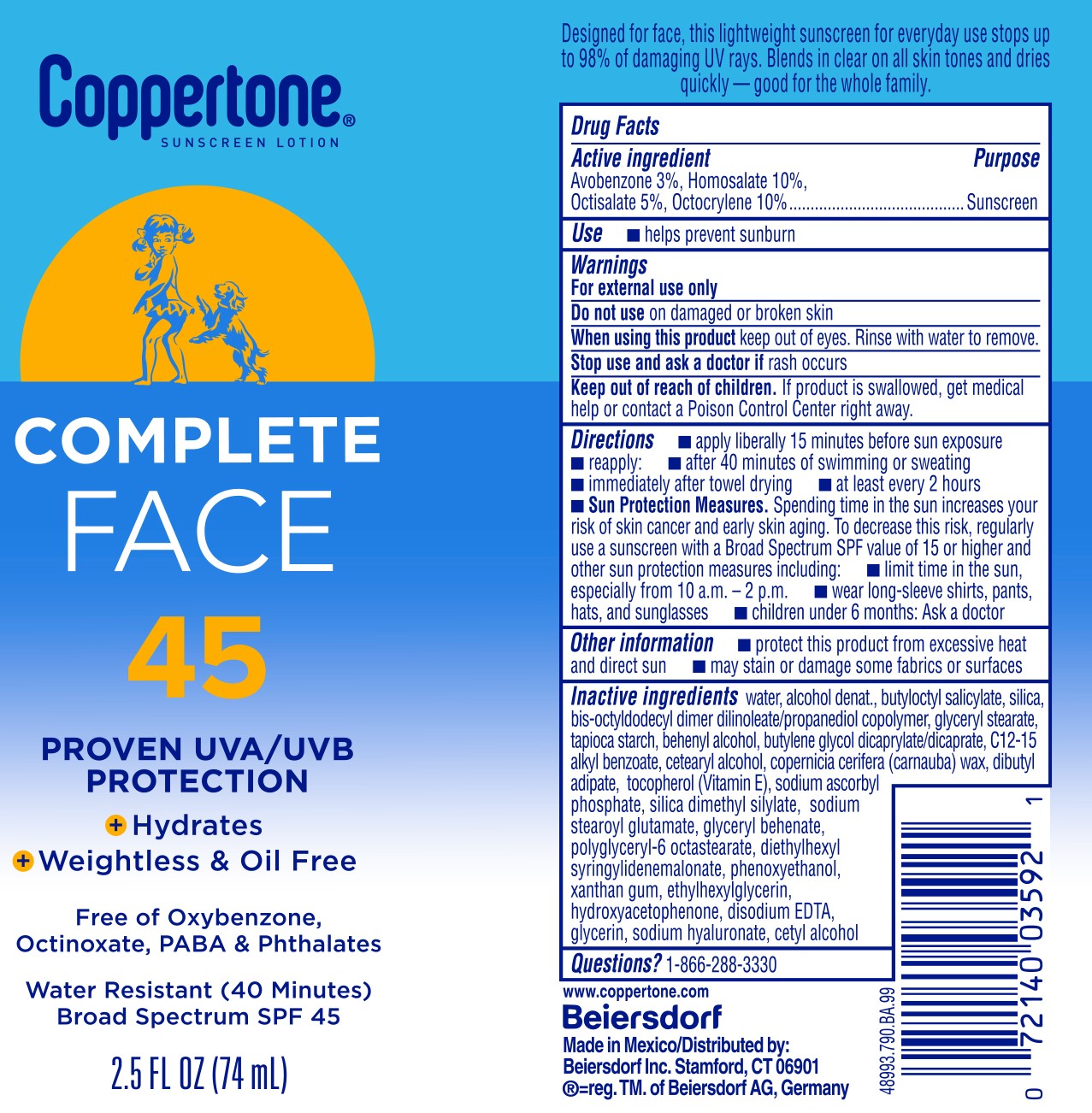 DRUG LABEL: Coppertone Complete Sunscreen SPF 45
NDC: 66800-8159 | Form: LOTION
Manufacturer: Beierdorf Inc
Category: otc | Type: HUMAN OTC DRUG LABEL
Date: 20251231

ACTIVE INGREDIENTS: HOMOSALATE 10 g/100 g; OCTISALATE 5 g/100 g; OCTOCRYLENE 10 g/100 g; AVOBENZONE 3 g/100 g
INACTIVE INGREDIENTS: BUTYLENE GLYCOL DICAPRYLATE/DICAPRATE; SODIUM ASCORBYL PHOSPHATE; XANTHAN GUM; HYDROXYACETOPHENONE; DISODIUM EDTA-COPPER; HYALURONATE SODIUM; CETOSTEARYL ALCOHOL; CARNAUBA WAX; DIBUTYL ADIPATE; TOCOPHEROL; DIETHYLHEXYL SYRINGYLIDENEMALONATE; GLYCERIN; ALCOHOL; BIS-OCTYLDODECYL DIMER DILINOLEATE/PROPANEDIOL COPOLYMER; GLYCERYL STEARATE SE; STARCH, TAPIOCA; SILICA DIMETHYL SILYLATE; WATER; BUTYLOCTYL SALICYLATE; TITANIUM DIOXIDE; BUTYLENE GLYCOL; ALKYL (C12-15) BENZOATE; CETYL ALCOHOL; DOCOSANOL; POLYGLYCERYL-6 STEARATE; PHENOXYETHANOL; ETHYLHEXYLGLYCERIN; DISODIUM STEAROYL GLUTAMATE; ETHYLHEXYLGLYCERYL BEHENATE

Complete Face Lotion SPF 45

Active ingredients

Avobenzone 3%, Homosalate 10%, Octisalate 5%, Octocrylene 10%

Purpose

Sunscreen

Use

■ helps prevent sunburn

Warnings

For external use only

Do not useon damaged or broken skin

WHEN USING

When using this productkeep out of eyes. Rinse with water to remove.

Stop use and ask a doctor ifrash occurs

Keep out of reach of children.If product is swallowed, get medical help or contact a Poison Control Center right away.

Directions

■ apply liberally 15 minutes before sun exposure

■ reapply:

■ after 40 minutes of swimming or sweating

■ immediately after towel drying

■ at least every 2 hours

■ Sun Protection Measures. Spending time in the sun increases your risk of skin cancer and early skin aging. To decrease this risk, regularly use a sunscreen with a Broad Spectrum SPF value of 15 or higher and other sun protection measures including:

■ limit time in the sun, especially from 10 a.m. – 2 p.m.

■ wear long-sleeve shirts, pants, hats, and sunglasses

■ children under 6 months: Ask a doctor

Other information

■ protect this product from excessive heat and direct sun

■ may stain or damage some fabrics or surfaces

Questions?

1-866-288-3330

Inactive ingredients

water, alcohol denat., butyloctyl salicylate, silica, bis-octyldodecyl dimer dilinoleate/propanediol copolymer, glyceryl stearate, tapioca starch, behenyl alcohol, butylene glycol dicaprylate/dicaprate, C12-15 alkyl benzoate, cetearyl alcohol, copernicia cerifera (carnauba) wax, dibutyl adipate, tocopherol (Vitamin E), sodium ascorbyl phosphate, silica dimethyl silylate, sodium stearoyl glutamate, glyceryl behenate, polyglyceryl-6 octastearate, diethylhexyl syringylidenemalonate, phenoxyethanol, xanthan gum, ethylhexylglycerin, hydroxyacetophenone, disodium EDTA, glycerin, sodium hyaluronate, cetyl alcohol

PACKAGE LABEL

Coppertone® Sunscreen Lotion

Complete Face 45

Proven UVA/UVB Protection

+Hydrates

+Weightless & Oil Free

Free of Oxybenzone, Octinoxate, Dyes & PABA

Water Resistant (40 Minutes)

Broad Spectrum SPF 45